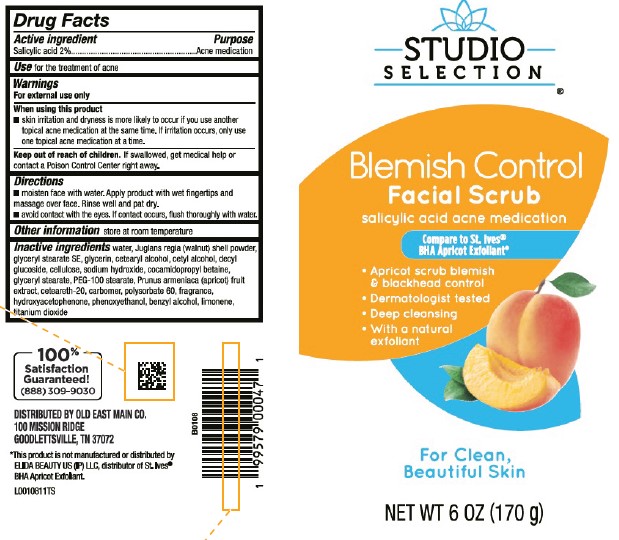 DRUG LABEL: Medicated Apricot Scrub
NDC: 55910-034 | Form: GEL
Manufacturer: Old East Main Co.
Category: otc | Type: HUMAN OTC DRUG LABEL
Date: 20260302

ACTIVE INGREDIENTS: SALICYLIC ACID 20 mg/1 g
INACTIVE INGREDIENTS: WATER; JUGLANS REGIA SHELL; GLYCERYL STEARATE SE; GLYCERIN; CETOSTEARYL ALCOHOL; CETYL ALCOHOL; DECYL GLUCOSIDE; POWDERED CELLULOSE; SODIUM HYDROXIDE; COCAMIDOPROPYL BETAINE; GLYCERYL MONOSTEARATE; PEG-100 STEARATE; APRICOT; POLYOXYL 20 CETOSTEARYL ETHER; CARBOMER HOMOPOLYMER, UNSPECIFIED TYPE; POLYSORBATE 60; HYDROXYACETOPHENONE; PHENOXYETHANOL; BENZYL ALCOHOL; LIMONENE, (+)-; TITANIUM DIOXIDE

Studio Selection 041.008/041AM
Medicated Apricot Scrub

Active ingredient

Salicylic acid 2%

Purpose

Acne medication

Use

for the treatment of acne

Warnings

For external use only

When using this product

- skin irritation and dryness is more likely to occur if you use another topical acne medication at the same time. If irritation occurs, only use one topical acne medication at a time.

Keep out of reach of children.

If swallowed, get medical help or contact a Poison Control Center right away.

Directions

- moisten face with water. Apply product with wet fingertips and massage over face. Rinse well and pat dry.
- avoid contact with the eyes. If contact occurs, flush thoroughly with water.

Other information

Store at room temperature

Inactive ingredients

water, Juglans regia (walnut) shell powder, glyceryl stearate SE, glycerin, cetearyl alcohol, cetyl alcohol, decyl glucoside, cellulose, sodium hydroxide, cocamidopropyl betaine, glyceryl stearate, PEG-100 stearate, Prunus armeniaca (apricot) fruit extract, ceteareth-20, carbomer, polysorbate 60, fragrance, hydroxyacetophenone, phenoxyethanol, benzyl alcohol, limonene, titanium dioxide

ADVERSE REACTION

100% Satisfaction Guaranteed!

(888)309-9030

DISTRIBUTED BY OLD EAST MAIN CO.

100 MISSION RIDGE

GOODLETTSVILLE, TN 37072

Disclaimer

*This product is not manufactured or distributed by ELIDA BEAUTY US (IP) LLC, distributor of St. Ives® BHA Apricot Exfoliant.

PRINCIPAL DISPLAY PANEL

STUDIO SELECTION®

Blemish Control

Facial Scrub

salicylic acid acne medication

Compare to St. Ives® BHA Apricot Exfoliant*

- Apricot scrub blemish & blackhead control
- Dermatologist tested
- Deep cleansing
- With natural exfoloants

For Clean, Beautiful Skin

NET WT 6 OZ (170 g)